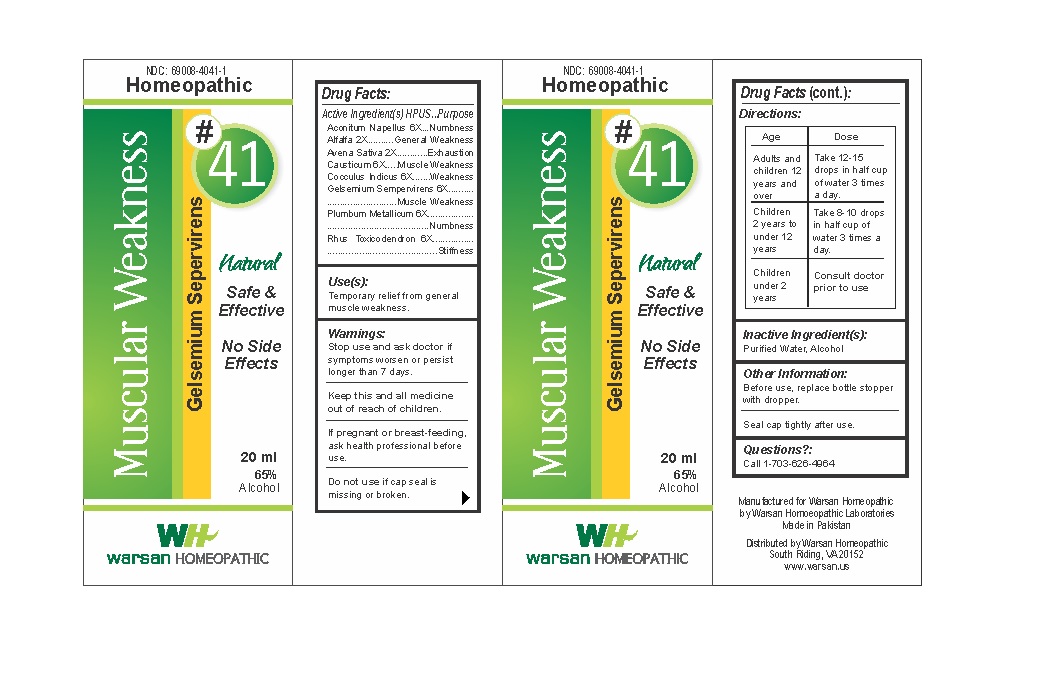 DRUG LABEL: Combination Remedy 41 - Muscular Weakness
NDC: 69008-4041 | Form: SOLUTION/ DROPS
Manufacturer: Warsan Homoeopathic Laboratories
Category: homeopathic | Type: HUMAN OTC DRUG LABEL
Date: 20171225

ACTIVE INGREDIENTS: AVENA SATIVA FLOWERING TOP 2 [hp_X]/1 mL; CAUSTICUM 6 [hp_X]/1 mL; ACONITUM NAPELLUS ROOT 6 [hp_X]/1 mL; GELSEMIUM SEMPERVIRENS ROOT 6 [hp_X]/1 mL; LEAD 6 [hp_X]/1 mL; ALFALFA 2 [hp_X]/1 mL; ANAMIRTA COCCULUS SEED 6 [hp_X]/1 mL; TOXICODENDRON PUBESCENS LEAF 6 [hp_X]/1 mL
INACTIVE INGREDIENTS: ALCOHOL; WATER

Stop use and ask doctor if symptoms worsen or persist longer than 7 days.

If pregnant or breast-feeding, ask health professional before use.

Do not use if tamper evident seal is missing or broken.

Keep out of reach of children.

ACTIVE INGREDIENT

Aconitum Napellus 6X

Alfalfa 2X

Avena Sativa 2X

Causticum 6X

Cocculus Indicus 6X

Gelsemium Sempervirens 6X

Plumbum Metallicum 6X

Rhus Toxicodendron 6X

PURPOSE

Temporary relief from general muscle weakness.

INACTIVE INGREDIENT

Purified Water

Alcohol

DOSAGE AND ADMINISTRATION

Adults and children 12 years and older: Take 10-15 drops in half cup of water 3 times a day.

Children 2 years to under 12 years: Take 8-10 drops in half cup of water of 3 times a day.

Children under 2 years: Consult doctor prior to use.

INDICATIONS AND USAGE

Temporary relief from general muscle weakness.